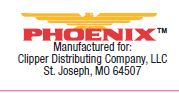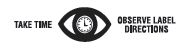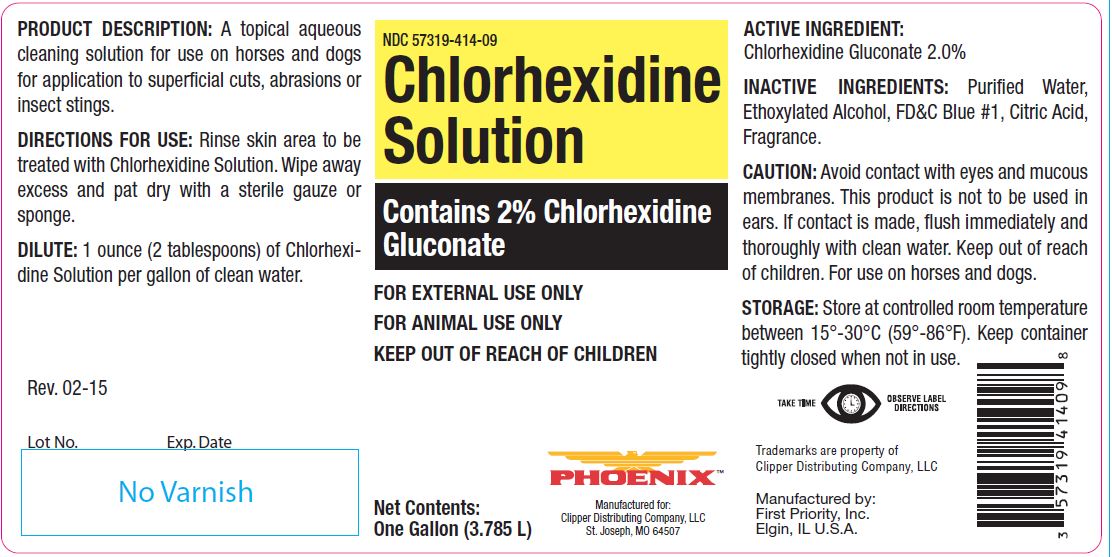 DRUG LABEL: Chlorhexidine
NDC: 57319-414 | Form: SOLUTION
Manufacturer: Clipper Distributing Company, LLC
Category: animal | Type: OTC ANIMAL DRUG LABEL
Date: 20191014

ACTIVE INGREDIENTS: CHLORHEXIDINE GLUCONATE 99.0 g/1 L

Chlorhexidine Solution

PURPOSE

Contains 2% Chlorhexidine Gluconate

KEEP OUT OF REACH OF CHILDREN

FOR EXTERNAL USE ONLY
FOR ANIMAL USE ONLY
KEEP OUT OF REACH OF CHILDREN

PRODUCT DESCRIPTION:

A topical aqueous cleaning solution for use on horses and dogs for application to superficial cuts, abrasions or insect stings.

DIRECTIONS FOR USE:

Rinse skin area to be treated with Chlorhexidine Solution. Wipe away excess and pat dry with a sterile gauze or sponge.

DILUTE:

1 ounce (2 tablespoons) of Chlorhexidine Solution per gallon of clean water.

ACTIVE INGREDIENT:

Chlorhexidine Gluconate 2.0%

INACTIVE INGREDIENTS:

Purified Water, Ethoxylated Alcohol, FD&C Blue #1, Citric Acid, Fragrance.

CAUTION:

Avoid contact with eyes and mucous membranes. This product is not to be used in ears. If contact is made, flush immediately and thoroughly with clean water. Keep out of reach of children. For use on horses and dogs.

STORAGE:

Store at controlled room temperature between 15°-30°C (59°-86°F). Keep container tightly closed when not in use.

Net Contents:

One Gallon (3.785 L)

INFORMATION FOR OWNERS/CAREGIVERS

Trademarks are property of Clipper Distributing Company, LLC

Manufactured by:
First Priority, Inc.
Elgin, IL U.S.A.